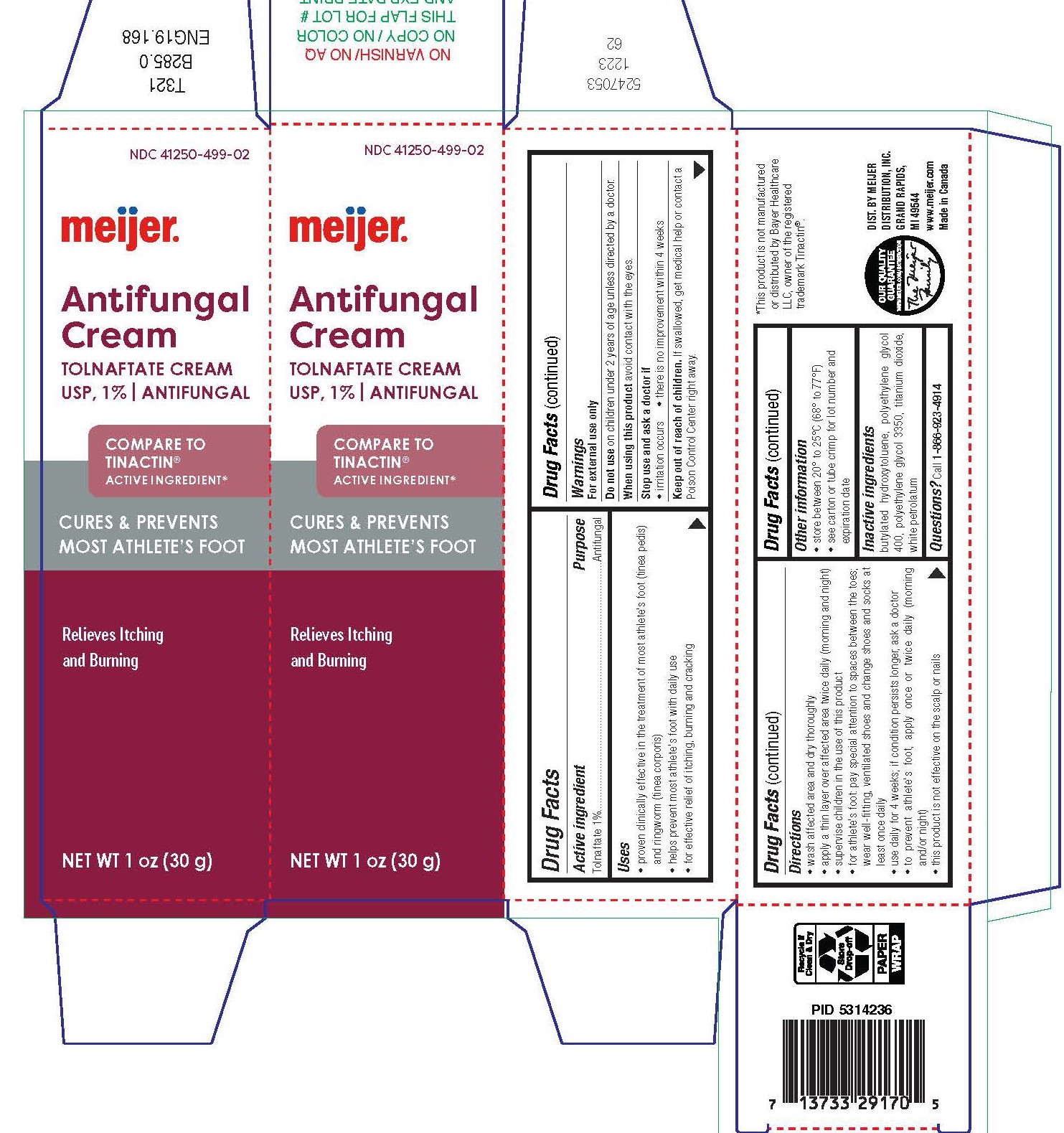 DRUG LABEL: meijer

NDC: 41250-499 | Form: CREAM
Manufacturer: Meijer Distribution Inc
Category: otc | Type: HUMAN OTC DRUG LABEL
Date: 20250702

ACTIVE INGREDIENTS: TOLNAFTATE 10 mg/1 g
INACTIVE INGREDIENTS: BUTYLATED HYDROXYTOLUENE; POLYETHYLENE GLYCOL 400; POLYETHYLENE GLYCOL 3350; TITANIUM DIOXIDE; PETROLATUM

meijer™
antifungal

Drug Facts

Active ingredient

Tolnaftate 1%

Purpose

Antifungal

Uses

- proven clinically effective in the treatment of most athlete's foot (tinea pedis) and ringworm (tinea corporis)
- helps prevent most athlete's foot with daily use
- for effective relief of itching, burning and cracking

Warnings

For external use only

Do not use

- on children under 2 years of age unless directed by a doctor.

When using this product

avoid contact with the eyes

Stop use and ask a doctor if

- irritation occurs
- there is no improvement within 4 weeks

Keep out of reach of children.If swallowed, get medical help or contact a Poison Control Center right away.

Directions

- wash affected area and dry thoroughly
- apply a thin layer over affected area twice daily (morning and night)
- supervise children in the use of this product
- for athlete's foot: pay special attention to spaces between the toes; wear well-fitting, ventilated shoes and change shoes and socks at least once daily
- use daily for 4 weeks; if condition persists longer, ask a doctor
- to prevent athlete's foot, apply once or twice daily (morning and/or night)
- this product is not effective on the scalp or nails

Other information

- store between 20° to 25°C (68° to 77°F)
- see carton or tube crimp for lot number and expiration date

Inactive ingredients

butylated hydroxytoluene, polyethylene glycol 400, polyethylene glycol 3350, titanium dioxide, white petrolatum

Questions?

Call 1-866-923-4914

DIST. BY MEIJER
DISTRIBUTION, INC.GRAND RAPIDS,
MI 49544
www.meijer.com
Made in Canada

PRINCIPAL DISPLAY PANEL - 15 g Tube Carton

meijer™

Cures & Prevents Most Athlete's Foot

AntifungalCream
Tolnaftate 1% Cream

NET WT 0.5 OZ (15 g)